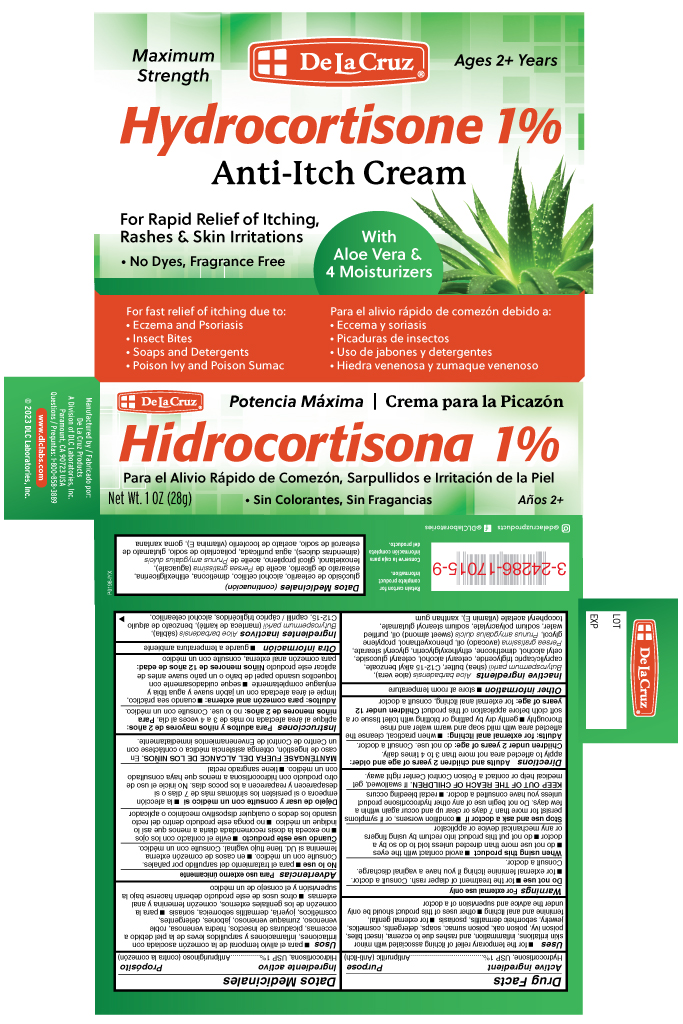 DRUG LABEL: Hydrocortisone 1% Anti-Itch Cream
NDC: 24286-1578 | Form: CREAM
Manufacturer: DLC Laboratories, Inc.
Category: otc | Type: HUMAN OTC DRUG LABEL
Date: 20260107

ACTIVE INGREDIENTS: HYDROCORTISONE 1 g/100 g
INACTIVE INGREDIENTS: ETHYLHEXYLGLYCERIN 0.2 g/100 g; SHEA BUTTER 1 g/100 g; ALOE VERA LEAF POLYSACCHARIDES 0.05 g/100 g; PROPYLENE GLYCOL 10 g/100 g; DIMETHICONE 0.8 g/100 g; SODIUM POLYACRYLATE (8000 MW) 0.6 g/100 g; CETYL ALCOHOL 2.5 g/100 g; CAPRYLIC/CAPRIC/LAURIC TRIGLYCERIDE 7 g/100 g; WATER 65.65 g/100 g; C12-20 ALKYL BENZOATE 4 g/100 g; ALMOND OIL 1 g/100 g; SODIUM STEAROYL GLUTAMATE 0.3 g/100 g; .ALPHA.-TOCOPHEROL ACETATE 0.1 g/100 g; CETEARYL GLUCOSIDE 2 g/100 g; PHENOXYETHANOL 0.9 g/100 g; AVOCADO OIL 0.1 g/100 g; XANTHAN GUM 0.3 g/100 g; GLYCERYL STEARATE SE 2.5 g/100 g

Hydrocortisone 1% Anti-Itch Cream

Drug Fact

Active Ingredient

Hydrocortisone, USP 1%

Purpose

Antipruitic (Anti-Itch)

Uses

for the temporary relief of itching associated with minor skin irritation, inflammation, and rashes due to eczema, insect bites, poison ivy, poison oak, poison sumac, soaps, detergents, cosmetics, jewelry, seborrheic dermatitis, psoriasis

for external genital, feminine and anal itching

other uses of this product should be only under the advice and supervision of a doctor

Warnings

For external use only

DO NOT USE

for the treatment of diaper rash. Consult a doctor.

for external feminine itching if you have a vaginal discharge. Consult a doctor.

When using this product

avoid contact with the eyes

do not use more than directed unless told to do so by a doctor

do not put this product into rectum by using fingers or any methanical devices or applicator

Stop use and ask a doctor if

condition worsens, or if symptoms persist for more than 7 days or clear up and occure again within a few days.

Do not begin use of any other hydrocotisone product unless you have consulted a doctor

rectal bleeding occurs

KEEP OUT OF THE REACH OF CHILDREN

If swallowed, get medical help or contact a Poison Control Center right away.

Directions

Adults and children 2 years of age and older: Apply to affected area not more than 3 to 4 times daily.

Children under 2 years of age: do not use. Consult a doctor.

Adults: for external anal itching: when practical, cleanse the affected area with mild soap and warm water and rinse thoroughly.

gently dry by patting or blotting with toilet tissue or a soft cloth before application of this product

Children under 12 years of age: for external anal itching, consult a doctor

Other information

Store at room temperature

Inactive ingredients

Aloe barbadensis (aloe vera), Butyrospermum parkii (shea) butter, C12-15 alkyl benzoate, caprylic/capric triglyceride, cetearyl alcohol, cetearyl glucoside, cetyl alcohol, dimethicone, ethylhexylglycerin, glyceryl stearate, Persea gratissima (avocado) oil, phenoxyethanol, propylene glycol, Prunus amygdalus dulcis (sweet almond) oil, purified water, sodium polyacrylate, sodium stearoyl glutamate, tocopheryl acetate (vitamin E), xanthan gum.

Questions

1-800-858-3889

dlclabs.com © 2023 DLC Laboratories, Inc.

Instagram: @delacruzproducts

Face Book @DLCLaboratories

Manufactured by

De La Cruz Products, A Division of DLC Laboratories, Inc. Paramount, CA 90723 USA

Principal Display

Maximum Strength

DeLaCruz®

Ages 2+ years

Hydrocortisone 1%

Anti-Itch Cream

For Rapid Relief of Itching,

Rashes & Skin Irritations

No Dyes, Fragrance Free

With Aloe Vera & 4 Moisturizer